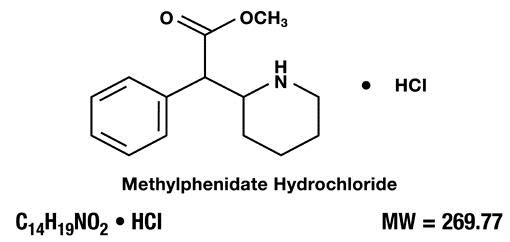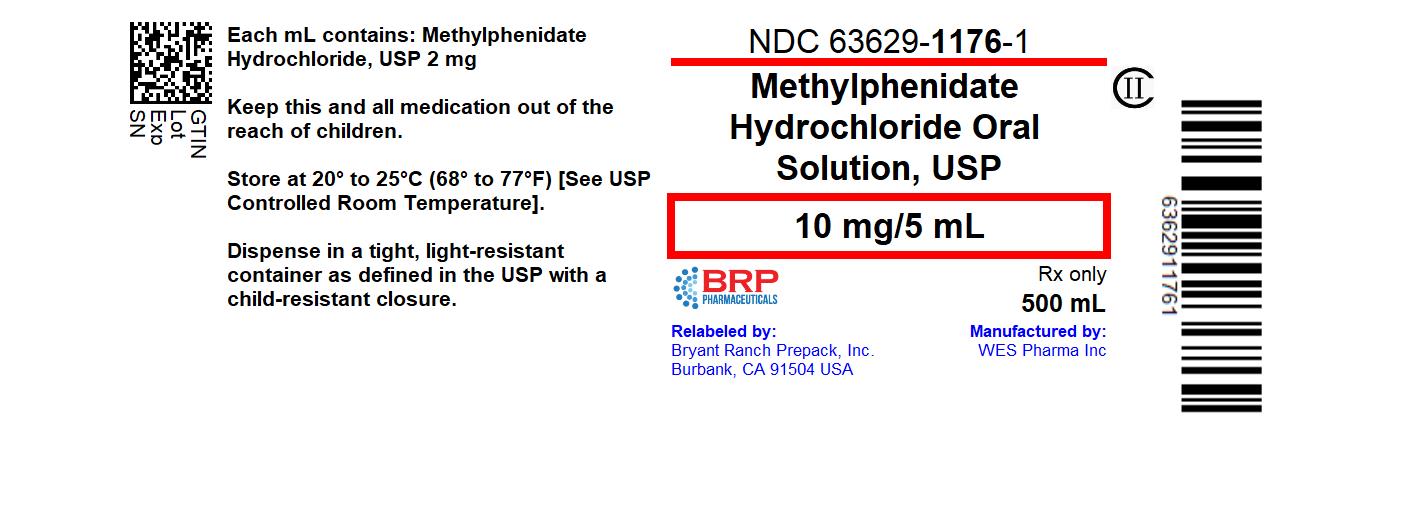 DRUG LABEL: Methylphenidate Hydrochloride
NDC: 63629-1176 | Form: SOLUTION
Manufacturer: Bryant Ranch Prepack
Category: prescription | Type: HUMAN PRESCRIPTION DRUG LABEL
Date: 20240110
DEA Schedule: CII

ACTIVE INGREDIENTS: METHYLPHENIDATE HYDROCHLORIDE 10 mg/5 mL
INACTIVE INGREDIENTS: GLYCERIN; WATER; POLYETHYLENE GLYCOL, UNSPECIFIED; HYDROCHLORIC ACID; GRAPE

Methylphenidate Hydrochloride Oral Solution, 5 mg/5 mL
Methylphenidate Hydrochloride Oral Solution, 10 mg/5 mL
CII
Rx only

DESCRIPTION

Methylphenidate hydrochloride oral solution is a mild central nervous system (CNS) stimulant available as 5 mg/5 mL and 10 mg/5 mL oral solutions for oral administration. Methylphenidate hydrochloride is methyl α-phenyl-2-piperidineacetate hydrochloride, and its structural formula is

Methylphenidate hydrochloride USP is a white to off white, fine crystalline powder. Its solutions are acid to litmus. It is freely soluble in water and in methanol, soluble in alcohol, and slightly soluble in chloroform and in acetone.
Each mL of methylphenidate hydrochloride oral solution 5 mg/5 mL contains 1 mg of methylphenidate hydrochloride USP.
Each mL of methylphenidate hydrochloride oral solution 10 mg/5 mL contains 2 mg of methylphenidate hydrochloride USP.
In addition, methylphenidate hydrochloride oral solution also contains the following inactive ingredients: glycerin,polyethylene glycol 1450, concord grape flavor N&A, diluted hydrochloric acid (10%), and purified water.

CLINICAL PHARMACOLOGY

Methylphenidate is a racemic mixture comprised of the d- and l-threo enantiomers. The d-threo enantiomer is more pharmacologically active than the l-threo enantiomer.
Methylphenidate HCl is a central nervous system (CNS) stimulant.
The mode of therapeutic action in humans is not completely understood, but methylphenidate presumably activates the brain stem arousal system and cortex to produce its stimulant effect. Methylphenidate is thought to block the reuptake of norepinephrine and dopamine into the presynaptic neuron and increase the release of these monoamines into the extraneuronal space.
There is neither specific evidence which clearly establishes the mechanism whereby methylphenidate hydrochloride oral solution produces its mental and behavioral effects in children, nor conclusive evidence regarding how these effects relate to the condition of the central nervous system.
Pharmacokinetics
Absorption
Methylphenidate hydrochloride oral solution, is readily absorbed. Following oral administration of methylphenidate hydrochloride oral solution, peak plasma methylphenidate concentrations are achieved at 1 to 2 hours. Methylphenidate hydrochloride oral solution, has been shown to be bioequivalent to Ritalin® tablet. The mean Cmax following a 20 mg dose is approximately 9 ng/mL.
Food Effect
In a study in adult volunteers to investigate the effects of a high-fat meal on the bioavailability of methylphenidate hydrochloride oral solution at a dose of 20 mg, the presence of food delayed the peak by approximately 1 hour (1.7 hours, fasted and 2.7 hours, fed). Overall, a high-fat meal increased the Cmax of methylphenidate hydrochloride oral solution by about 13% and the AUC by about 25%, on average. Through a cross-study comparison, the magnitude of increase in Cmax and AUC is found to be comparable between the methylphenidate hydrochloride oral solution, and Ritalin, the immediate release tablet.
Metabolism and Excretion
In humans, methylphenidate is metabolized primarily via deesterification to alpha-phenylpiperidine acetic acid (PPA, ritalinic acid). The metabolite has little or no pharmacologic activity.
After oral dosing of radiolabeled methylphenidate in humans, about 90% of the radioactivity was recovered in urine. The main urinary metabolite was PPA, accounting for approximately 80% of the dose.
The pharmacokinetics of the methylphenidate hydrochloride oral solution have been studied in healthy adult volunteers. The mean terminal half-life (t½) of methylphenidate following administration of 20 mg methylphenidate hydrochloride oral solution (t½ = 2.7 hours) is comparable to the mean terminal t½ following administration of Ritalin (methylphenidate hydrochloride immediate-release tablets) (t½ = 2.8h) in healthy adult volunteers.
Special Populations
Gender – The effect of gender on the pharmacokinetics of methylphenidate after methylphenidate hydrochloride oral solution administration has not been studied.
Race – The influence of race on the pharmacokinetics of methylphenidate after methylphenidate hydrochloride oral solution administration has not been studied.
Age – The pharmacokinetics of methylphenidate after methylphenidate hydrochloride oral solution administration have not been studied in pediatrics.
Renal Insufficiency
There is no experience with the use of methylphenidate hydrochloride oral solution in patients with renal insufficiency. After oral administration of radiolabeled methylphenidate in humans, methylphenidate was extensively metabolized and approximately 80% of the radioactivity was excreted in the urine in the form of ritalinic acid. Since renal clearance is not an important route of methylphenidate clearance, renal insufficiency is expected to have little effect on the pharmacokinetics of methylphenidate hydrochloride oral solution
Hepatic Insufficiency
There is no experience with the use of methylphenidate hydrochloride oral solution in patients with hepatic insufficiency.

INDICATIONS AND USAGE

Attention Deficit Disorders, Narcolepsy
Attention Deficit Disorders (previously known as Minimal Brain Dysfunction in Children). Other terms being used to describe the behavioral syndrome below include: Hyperkinetic Child Syndrome, Minimal Brain Damage, Minimal Cerebral Dysfunction, Minor Cerebral Dysfunction.
Methylphenidate hydrochloride oral solution is indicated as an integral part of a total treatment program which typically includes other remedial measures (psychological, educational, social) for a stabilizing effect in children with a behavioral syndrome characterized by the following group of developmentally inappropriate symptoms: moderate-to-severe distractibility, short attention span, hyperactivity, emotional lability, and impulsivity. The diagnosis of this syndrome should not be made with finality when these symptoms are only of comparatively recent origin. Nonlocalizing (soft) neurological signs, learning disability, and abnormal EEG may or may not be present, and a diagnosis of central nervous system dysfunction may or may not be warranted.
Special Diagnostic Considerations
Specific etiology of this syndrome is unknown, and there is no single diagnostic test. Adequate diagnosis requires the use not only of medical but of special psychological, educational, and social resources.
Characteristics commonly reported include: chronic history of short attention span, distractibility, emotional lability, impulsivity, and moderate-to-severe hyperactivity; minor neurological signs and abnormal EEG. Learning may or may not be impaired. The diagnosis must be based upon a complete history and evaluation of the child and not solely on the presence of one or more of these characteristics.
Drug treatment is not indicated for all children with this syndrome. Stimulants are not intended for use in the child who exhibits symptoms secondary to environmental factors and/or primary psychiatric disorders, including psychosis. Appropriate educational placement is essential and psychosocial intervention is generally necessary. When remedial measures alone are insufficient, the decision to prescribe stimulant medication will depend upon the physician’s assessment of the chronicity and severity of the child’s symptoms.

CONTRAINDICATIONS

Marked anxiety, tension, and agitation are contraindications to methylphenidate hydrochloride oral solution, since the drug may aggravate these symptoms. Methylphenidate hydrochloride oral solution is contraindicated also in patients known to be hypersensitive to the drug, in patients with glaucoma, and in patients with motor tics or with a family history or diagnosis of Tourette’s syndrome.
Methylphenidate Hydrochloride Oral Solution is contraindicated during treatment with monoamine oxidase inhibitors, and also within a minimum of 14 days following discontinuation of a monoamine oxidase inhibitor (hypertensive crises may result).

WARNINGS

Serious Cardiovascular Events
Sudden Death and Pre-Existing Structural Cardiac Abnormalities or Other Serious Heart Problems
Children and Adolescents – Sudden death has been reported in association with CNS stimulant treatment at usual doses in children and adolescents with structural cardiac abnormalities or other serious heart problems. Although some serious heart problems alone carry an increased risk of sudden death, stimulant products generally should not be used in children or adolescents with known serious structural cardiac abnormalities, cardiomyopathy, serious heart rhythm abnormalities, or other serious cardiac problems that may place them at increased vulnerability to the sympathomimetic effects of a stimulant drug.
Adults – Sudden deaths, stroke, and myocardial infarction have been reported in adults taking stimulant drugs at usual doses for ADHD. Although the role of stimulants in these adult cases is also unknown, adults have a greater likelihood than children of having serious structural cardiac abnormalities, cardiomyopathy, serious heart rhythm abnormalities, coronary artery disease, or other serious cardiac problems. Adults with such abnormalities should also generally not be treated with stimulant drugs.
Hypertension and Other Cardiovascular Conditions
Stimulant medications cause a modest increase in average blood pressure (about 2 to 4 mmHg) and average heart rate (about 3 to 6 bpm), and individuals may have larger increases. While the mean changes alone would not be expected to have short-term consequences, all patients should be monitored for larger changes in heart rate and blood pressure. Caution is indicated in treating patients whose underlying medical conditions might be compromised by increases in blood pressure or heart rate, e.g., those with pre-existing hypertension, heart failure, recent myocardial infarction, or ventricular arrhythmia.
Assessing Cardiovascular Status in Patients being Treated with Stimulant Medications
Children, adolescents, or adults who are being considered for treatment with stimulant medications should have a careful history (including assessment for a family history of sudden death or ventricular arrhythmia) and physical exam to assess for the presence of cardiac disease, and should receive further cardiac evaluation if findings suggest such disease (e.g., electrocardiogram and echocardiogram). Patients who develop symptoms such as exertional chest pain, unexplained syncope, or other symptoms suggestive of cardiac disease during stimulant treatment should undergo a prompt cardiac evaluation.
Psychiatric Adverse Events
Pre-Existing Psychosis – Administration of stimulants may exacerbate symptoms of behavior disturbance and thought disorder in patients with a pre-existing psychotic disorder.
Bipolar Illness – Particular care should be taken in using stimulants to treat ADHD in patients with comorbid bipolar disorder because of concern for possible induction of a mixed/manic episode in such patients. Prior to initiating treatment with a stimulant, patients with comorbid depressive symptoms should be adequately screened to determine if they are at risk for bipolar disorder; such screening should include a detailed psychiatric history, including a family history of suicide, bipolar disorder, and depression.
Emergence of New Psychotic or Manic Symptoms – Treatment emergent psychotic or manic symptoms, e.g., hallucinations, delusional thinking, or mania in children and adolescents without a prior history of psychotic illness or mania can be caused by stimulants at usual doses. If such symptoms occur, consideration should be given to a possible causal role of the stimulant, and discontinuation of treatment may be appropriate. In a pooled analysis of multiple short-term, placebo-controlled studies, such symptoms occurred in about 0.1% (4 patients with events out of 3,482 exposed to methylphenidate or amphetamine for several weeks at usual doses) of stimulant-treated patients compared to 0 in placebo-treated patients.
Aggression – Aggressive behavior or hostility is often observed in children and adolescents with ADHD, and has been reported in clinical trials and the postmarketing experience of some medications indicated for the treatment of ADHD. Although there is no systematic evidence that stimulants cause aggressive behavior or hostility, patients beginning treatment for ADHD should be monitored for the appearance of or worsening of aggressive behavior or hostility.
Seizures
There is some clinical evidence that stimulants may lower the convulsive threshold in patients with prior history of seizures, in patients with prior EEG abnormalities in absence of seizures, and, very rarely, in patients without a history of seizures and no prior EEG evidence of seizures. In the presence of seizures, the drug should be discontinued.
Priapism
Prolonged and painful erections, sometimes requiring surgical intervention, have been reported with methylphenidate products in both pediatric and adult patients. Priapism was not reported with drug initiation but developed after some time on the drug, often subsequent to an increase in dose. Priapism has also appeared during a period of drug withdrawal (drug holidays or discontinuation): Patients who develop abnormally sustained or frequent and painful erections should seek immediate medical attention.
Peripheral Vasculopathy, Including Raynaud’s Phenomenon
Stimulants, including methylphenidate hydrochloride oral solution, used to treat ADHD are associated with peripheral vasculopathy, including Raynaud’s phenomenon. Signs and symptoms are usually intermittent and mild; however, very rare sequelae include digital ulceration and/or soft tissue breakdown. Effects of peripheral vasculopathy, including Raynaud’s phenomenon, were observed in post-marketing reports at different times and at therapeutic doses in all age groups throughout the course of treatment. Signs and symptoms generally improve after reduction in dose or discontinuation of drug. Careful observation for digital changes is necessary during treatment with ADHD stimulants. Further clinical evaluation (e.g., rheumatology referral) may be appropriate for certain patients.
Long-Term Suppression of Growth
Careful follow-up of weight and height in children ages 7 to 10 years who were randomized to either methylphenidate or non-medication treatment groups over 14 months, as well as in naturalistic subgroups of newly methylphenidate-treated and non-medication treated children over 36 months (to the ages of 10 to 13 years), suggests that consistently medicated children (i.e., treatment for 7 days per week throughout the year) have a temporary slowing in growth rate (on average, a total of about 2 cm less growth in height and 2.7 kg less growth in weight over 3 years), without evidence of growth rebound during this period of development.
Published data are inadequate to determine whether chronic use of amphetamines may cause a similar suppression of growth, however, it is anticipated that they likely have this effect as well. Therefore, growth should be monitored during treatment with stimulants, and patients who are not growing or gaining height or weight as expected may need to have their treatment interrupted.
Visual Disturbance
Difficulties with accommodation and blurring of vision have been reported with stimulant treatment.
USE IN CHILDREN LESS THAN SIX YEARS OF AGE
Methylphenidate hydrochloride oral solution should not be used in children under six years, since safety and efficacy in this age group have not been established.

DRUG ABUSE AND DEPENDENCE
Methylphenidate Hydrochloride Oral Solution should be given cautiously to emotionally unstable patients, such as those with a history of drug dependence or alcoholism, because such patients may increase dosage on their own initiative.
Chronically abusive use can lead to marked tolerance and psychic dependence with varying degrees of abnormal behavior. Frank psychotic episodes can occur, especially with parenteral abuse. Careful supervision is required during drug withdrawal, since severe depression as well as the effects of chronic overactivity can be unmasked. Long-term follow-up may be required because of the patient’s basic personality disturbances.

PRECAUTIONS

General

Patients with an element of agitation may react adversely; discontinue therapy if necessary.
Periodic CBC, differential, and platelet counts are advised during prolonged therapy.
Drug treatment is not indicated in all cases of this behavioral syndrome and should be considered only in light of the complete history and evaluation of the child. The decision to prescribe methylphenidate hydrochloride oral solution should depend on the physician’s assessment of the chronicity and severity of the child’s symptoms and their appropriateness for his/her age. Prescription should not depend solely on the presence of one or more of the behavioral characteristics.
When these symptoms are associated with acute stress reactions, treatment with methylphenidate hydrochloride oral solution is usually not indicated.
Long-term effects of methylphenidate hydrochloride oral solution in children have not been well established.

Information for Patients

Prescribers or other health professionals should inform patients, their families, and their caregivers about the benefits and risks associated with treatment with methylphenidate and should counsel them in its appropriate use. A patient Medication Guide is available for methylphenidate hydrochloride oral solution. The prescriber or health professional should instruct patients, their families, and their caregivers to read the Medication Guide and should assist them in understanding its contents. Patients should be given the opportunity to discuss the contents of the Medication Guide and to obtain answers to any questions they may have. The complete text of the Medication Guide is reprinted at the end of this document.
Priapism
Advise patients, caregivers, and family members of the possibility of painful or prolonged penile erections (priapism). Instruct the patient to seek immediate medical attention in the event of priapism.
Circulation Problems in Fingers and Toes [Peripheral Vasculopathy, Including Raynaud’s Phenomenon]
• Instruct patients beginning treatment with methylphenidate hydrochloride oral solution about the risk of peripheral vasculopathy, including Raynaud’s Phenomenon, and associated signs and symptoms: fingers or toes may feel numb, cool, painful, and/or may change color from pale, to blue, to red.
• Instruct patients to report to their physician any new numbness, pain, skin color change, or sensitivity to temperature in fingers or toes.
• Instruct patients to call their physician immediately with any signs of unexplained wounds appearing on fingers or toes while taking methylphenidate hydrochloride oral solution.
• Further clinical evaluation (e.g., rheumatology referral) may be appropriate for certain patients.

Drug Interactions

Methylphenidate hydrochloride oral solution may decrease the hypotensive effect of guanethidine. Use cautiously with pressor agents.
Human pharmacologic studies have shown that methylphenidate hydrochloride oral solution may inhibit the metabolism of coumarin anticoagulants, anticonvulsants (phenobarbital, diphenylhydantoin, primidone), phenylbutazone, and tricyclic drugs (imipramine, clomipramine, desipramine). Downward dosage adjustments of these drugs may be required when given concomitantly with methylphenidate hydrochloride oral solution.

Carcinogenesis, Mutagenesis, Impairment of Fertility

In a lifetime carcinogenicity study carried out in B6C3F1 mice, methylphenidate caused an increase in hepatocellular adenomas and, in males only, an increase in hepatoblastomas, at a daily dose of approximately 60 mg/kg/day. This dose is approximately 30 times and 2.5 times the maximum recommended human dose on a mg/kg and mg/m^2 basis, respectively. Hepatoblastoma is a relatively rare rodent malignant tumor type. There was no increase in total malignant hepatic tumors. The mouse strain used is sensitive to the development of hepatic tumors, and the significance of these results to humans is unknown.
Methylphenidate did not cause any increase in tumors in a lifetime carcinogenicity study carried out in F344 rats; the highest dose used was approximately 45 mg/kg/day, which is approximately 22 times and 4 times the maximum recommended human dose on a mg/kg and mg/m^2 basis, respectively.
Methylphenidate was not mutagenic in the in vitro Ames reverse mutation assay or in the in vitro mouse lymphoma cell forward mutation assay. Sister chromatid exchanges and chromosome aberrations were increased, indicative of a weak clastogenic response, in an in vitro assay in cultured Chinese Hamster Ovary (CHO) cells. The genotoxic potential of methylphenidate has not been evaluated in an in vivo assay.

Usage in Pregnancy

Adequate animal reproduction studies to establish safe use of methylphenidate hydrochloride oral solution during pregnancy have not been conducted. However, in a recently conducted study, methylphenidate has been shown to have teratogenic effects in rabbits when given in doses of 200 mg/kg/day, which is approximately 167 times and 78 times the maximum recommended human dose on a mg/kg and a mg/m^2 basis, respectively. In rats, teratogenic effects were not seen when the drug was given in doses of 75 mg/kg/day, which is approximately 62.5 and 13.5 times the maximum recommended human dose on a mg/kg and a mg/m^2 basis, respectively. Therefore, until more information is available, methylphenidate should not be prescribed for women of childbearing age unless, in the opinion of the physician, the potential benefits outweigh the possible risks.

ADVERSE REACTIONS

Nervousness and insomnia are the most common adverse reactions but are usually controlled by reducing dosage and omitting the drug in the afternoon or evening. Other reactions include hypersensitivity (including skin rash, urticaria, fever, arthralgia, exfoliative dermatitis, erythema multiforme with histopathological findings of necrotizing vasculitis, and thrombocytopenic purpura); anorexia; nausea; dizziness; palpitations; headache; dyskinesia; drowsiness; blood pressure and pulse changes, both up and down; tachycardia; angina; cardiac arrhythmia; abdominal pain; weight loss during prolonged therapy; libido changes; and rhabdomyolysis. There have been rare reports of Tourette’s syndrome. Toxic psychosis has been reported. Although a definite causal relationship has not been established, the following have been reported in patients taking this drug: instances of abdominal liver function, ranging from transaminase elevation to severe hepatic injury; isolated cases of cerebral arteritis and/or occlusion; leukopenia and/or anemia; transient depressed mood; a few instances of scalp hair loss; serotonin syndrome in combination with serotonergic drugs. Very rare reports of neuroleptic malignant syndrome (NMS) have been received, and, in most of these, patients were concurrently receiving therapies associated with NMS. In a single report, a ten year old boy who had been taking methylphenidate for approximately 18 months experienced an NMS-like event within 45 minutes of ingesting his first dose of venlafaxine. It is uncertain whether this case represented a drug-drug interaction, a response to either drug alone, or some other cause.
In children, loss of appetite, abdominal pain, weight loss during prolonged therapy, insomnia, and tachycardia may occur more frequently; however, any of the other adverse reactions listed above may also occur.

OVERDOSAGE

Signs and symptoms of acute overdosage, resulting principally from overstimulation of the central nervous system and from excessive sympathomimetic effects, may include the following: vomiting, agitation, tremors, hyperreflexia, muscle twitching, convulsions (may be followed by coma), euphoria, confusion, hallucinations, delirium, sweating, flushing, headache, hyperpyrexia, tachycardia, palpitations, cardiac arrhythmias, hypertension, mydriasis, dryness of mucous membranes, and rhabdomyolysis.
Consult with a Certified Poison Control Center regarding treatment for up-to-date guidance and advice.
Treatment consists of appropriate supportive measures. The patient must be protected against self-injury and against external stimuli that would aggravate overstimulation already present. Gastric contents may be evacuated by gastric lavage. In the presence of severe intoxication, use a carefully titrated dosage of a short-acting barbiturate before performing gastric lavage. Other measures to detoxify the gut include administration of activated charcoal and a cathartic.
Intensive care must be provided to maintain adequate circulation and respiratory exchange; external cooling procedures may be required for hyperpyrexia.
Efficacy of peritoneal dialysis or extracorporeal hemodialysis for methylphenidate overdosage has not been established.

DOSAGE AND ADMINISTRATION

Dosage should be individualized according to the needs and responses of the patient.
Adults
Administer in divided doses 2 or 3 times daily, preferably 30 to 45 minutes before meals. Average dosage is 20 to 30 mg daily. Some patients may require 40 to 60 mg daily. In others, 10 to 15 mg daily will be adequate. Patients who are unable to sleep if medication is taken late in the day should take the last dose before 6 p.m.
Children (6 years and over)
Methylphenidate hydrochloride oral solution should be initiated in small doses, with gradual weekly increments. Daily dosage above 60 mg is not recommended.
If improvement is not observed after appropriate dosage adjustment over a one-month period, the drug should be discontinued.
Start with 5 mg twice daily (before breakfast and lunch) with gradual increments of 5 to 10 mg weekly.
If paradoxical aggravation of symptoms or other adverse effects occur, reduce dosage, or, if necessary, discontinue the drug.
Methylphenidate hydrochloride oral solution should be periodically discontinued to assess the child’s condition. Improvement may be sustained when the drug is either temporarily or permanently discontinued.
Drug treatment should not and need not be indefinite and usually may be discontinued after puberty.

HOW SUPPLIED

Methylphenidate Hydrochloride Oral Solution is a clear, colorless to pale yellow, grape flavored solution with no visible particulates.

• 10 mg per 5 mL
Bottles of 500 mL……… NDC 63629-1176-1

Storage and Handling
Store at 20° to 25°C (68° to 77°F) [see USP Controlled Room Temperature]. Dispense in tight container with child-resistant closure.

Disposal
Comply with local laws and regulations on drug disposal of CNS stimulants. Dispose of remaining, unused, or expired methylphenidate hydrochloride oral solution by a medicine take-back program or by an authorized collector registered with the Drug Enforcement Administration. If no take-back program or authorized collector is available, mix methylphenidate hydrochloride oral solution with an undesirable, nontoxic substance to make it less appealing to children and pets. Place the mixture in a container such as a sealed plastic bag and discard methylphenidate hydrochloride oral solution in the household trash.

Repackaged/Relabeled by:
Bryant Ranch Prepack, Inc.
Burbank, CA 91504

MEDICATION GUIDE

Methylphenidate (METH-il-FEN-i-date) Hydrochloride Oral Solution, 5 mg/5 mL and 10 mg/5 mL
CII
Read the Medication Guide that comes with methylphenidate hydrochloride oral solution before you or your child starts taking it and each time you get a refill. There may be new information. This Medication Guide does not take the place of talking to your doctor about your or your child’s treatment with methylphenidate hydrochloride oral solution.

What is the most important information I should know about methylphenidate hydrochloride oral solution?
The following have been reported with use of methylphenidate HCl oral solution and other stimulant medicines.
1. Heart-related problems:
• sudden death in patients who have heart problems or heart defects
• stroke and heart attack in adults
• increased blood pressure and heart rate
Tell your doctor if you or your child have any heart problems, heart defects, high blood pressure, or a family history of these problems.
Your doctor should check you or your child carefully for heart problems before starting methylphenidate hydrochloride oral solution.
Your doctor should check you or your child’s blood pressure and heart rate regularly during treatment with methylphenidate hydrochloride oral solution.
Call your doctor right away if you or your child has any signs of heart problems such as chest pain, shortness of breath, or fainting while taking methylphenidate hydrochloride oral solution.
2. Mental (Psychiatric) problems:
All Patients
• new or worse behavior and thought problems
• new or worse bipolar illness
• new or worse aggressive behavior or hostility
Children and Teenagers
• new psychotic symptoms (such as hearing voices, believing things that are not true, are suspicious) or new manic symptoms
Tell your doctor about any mental problems you or your child have, or about a family history of suicide, bipolar illness, or depression.
Call your doctor right away if you or your child have any new or worsening mental symptoms or problems while taking methylphenidate hydrochloride oral solution, especially seeing or hearing things that are not real, believing things that are not real, or are suspicious.
3. Circulation problems in fingers and toes [Peripheral vasculopathy, including Raynaud’s phenomenon]: fingers or toes may feel numb, cool, painful, and/or may change color from pale, to blue, to red.
• Tell your doctor if you have or your child has numbness, pain, skin color change, or sensitivity to temperature in your fingers or toes.
• Call your doctor right away if you have or your child has any signs of unexplained wounds appearing on fingers or toes while taking methylphenidate hydrochloride oral solution.

What Is methylphenidate hydrochloride oral solution?
Methylphenidate hydrochloride oral solution is a central nervous system stimulant prescription medicine. Methylphenidate hydrochloride oral solution is a liquid form of medication that you take by mouth. It is used for the treatment of Attention-Deficit Hyperactivity Disorder (ADHD).
Methylphenidate hydrochloride oral solution may help increase attention and decrease impulsiveness and hyperactivity in patients with ADHD.
Methylphenidate hydrochloride oral solution should be used as a part of a total treatment program for ADHD that may include counseling or other therapies.
Methylphenidate hydrochloride oral solution is also used in the treatment of a sleep disorder called narcolepsy.

Methylphenidate hydrochloride oral solution is a federally controlled substance (CII) because it can be abused or lead to dependence. Keep methylphenidate hydrochloride oral solution in a safe place to prevent misuse and abuse. Selling or giving away methylphenidate hydrochloride oral solution may harm others, and is against the law.
Tell your doctor if you or your child have (or have a family history of) ever abused or been dependent on alcohol, prescription medicines or street drugs.

Who should not take methylphenidate hydrochloride oral solution?
Methylphenidate Hydrochloride Oral Solution should not be taken if you or your child:
• are very anxious, tense, or agitated
• have an eye problem called glaucoma
• have tics or Tourette’s syndrome, or a family history of Tourette’s syndrome. Tics are hard to control repeated movements or sounds.
• are taking or have taken within the past 14 days an antidepression medicine called a monoamine oxidase inhibitor or MAOI.
• are allergic to anything in methylphenidate hydrochloride oral solution. See the end of this Medication Guide for a complete list of ingredients.
Methylphenidate hydrochloride oral solution should not be used in children less than 6 years old because it has not been studied in this age group.
Methylphenidate hydrochloride oral solution may not be right for you or your child. Before starting methylphenidate hydrochloride oral solution tell your or your child’s doctor about all health conditions (or a family history of) including:
• heart problems, heart defects, high blood pressure
• mental problems including psychosis, mania, bipolar illness, or depression
• tics or Tourette’s syndrome
• seizures or have had an abnormal brain wave test (EEG)
• circulation problems in fingers and toes
Tell your doctor if you or your child is pregnant, planning to become pregnant, or breastfeeding.
Can methylphenidate hydrochloride oral solution be taken with other medicines?
Tell your doctor about all of the medicines that you or your child take including prescription and nonprescription medicines, vitamins, and herbal supplements.
Methylphenidate hydrochloride oral solution and some medicines may interact with each other and cause serious side effects. Sometimes the doses of other medicines will need to be adjusted while taking methylphenidate hydrochloride oral solution.
Your doctor will decide whether methylphenidate hydrochloride oral solution can be taken with other medicines.
Especially tell your doctor if you or your child takes:
• antidepression medicines including MAOIs
• seizure medicines
• blood thinner medicines
• blood pressure medicines
• cold or allergy medicines that contain decongestants
Know the medicines that you or your child takes. Keep a list of your medicines with you to show your doctor and pharmacist.
Do not start any new medicine while taking methylphenidate hydrochloride oral solution without talking to your doctor first.
How should methylphenidate hydrochloride oral solution be taken?

• Take methylphenidate hydrochloride oral solution exactly as prescribed. Your doctor may adjust the dose until it is right for you or your child.
• Methylphenidate Hydrochloride Oral Solution is usually taken 2 to 3 times a day.
• Take methylphenidate hydrochloride oral solution 30 to 45 minutes before meals.
• From time to time, your doctor may stop methylphenidate hydrochloride oral solution treatment for a while to check ADHD symptoms.
• Your doctor may do regular checks of the blood, heart, and blood pressure while taking methylphenidate hydrochloride oral solution. Children should have their height and weight checked often while taking methylphenidate hydrochloride oral solution. Methylphenidate Hydrochloride Oral Solution treatment may be stopped if a problem is found during these check-ups.
• If you or your child takes too much methylphenidate hydrochloride oral solution or overdoses, call your doctor or poison control center right away, or get emergency treatment.
What are possible side effects of methylphenidate hydrochloride oral solution?
See “What is the most important information I should know about methylphenidate hydrochloride oral solution?” for information on reported heart and mental problems.
Other serious side effects include:
• slowing of growth (height and weight) in children
• seizures, mainly in patients with a history of seizures
• eyesight changes or blurred vision
• Painful and prolonged erections (priapism) have occurred with methylphenidate. If you or your child develop priapism, seek medical help right away. Because of the potential for lasting damage, priapism should be evaluated by a doctor immediately.
Common side effects include:
• nervousness
• trouble sleeping
• headache
• stomach ache
• fast heart beat
• nausea
• decreased appetite
• dizziness
• weight loss
Talk to your doctor if you or your child has side effects that are bothersome or do not go away.
This is not a complete list of possible side effects. Ask your doctor or pharmacist for more information.
Call your doctor for medical advice about side effects. You may report side effects to FDA at 1-800-FDA-1088.
How should I store methylphenidate hydrochloride oral solution?
• Store methylphenidate hydrochloride oral solution in a safe place at room temperature, 68° to 77°F (20° to 25°C).
• Keep methylphenidate hydrochloride oral solution and all medicines out of the reach of children.
General information about methylphenidate hydrochloride oral solution
Medicines are sometimes prescribed for purposes other than those listed in a Medication Guide. Do not use methylphenidate hydrochloride oral solution for a condition for which it was not prescribed. Do not give methylphenidate hydrochloride oral solution to other people, even if they have the same condition. It may harm them and it is against the law.
This Medication Guide summarizes the most important information about methylphenidate hydrochloride oral solution. If you would like more information, talk with your doctor. You can ask your doctor or pharmacist for information about methylphenidate hydrochloride oral solution that was written for healthcare professionals. For more information, please contact WES Pharma Inc at 1-888-212-6921.
What are the ingredients in methylphenidate hydrochloride oral solution?
Active Ingredient: methylphenidate hydrochloride USP
Inactive Ingredients: glycerin, polyethylene glycol 1450, concord grape flavor N&A, diluted hydrochloric acid (10%), and purified water.
This Medication Guide has been approved by the U.S. Food and Drug Administration.
Distributed by:
Eywa Pharma Inc
2 Research Way, Floor 3
Princeton, NJ 08540
Manufactured by:
WES Pharma Inc
Westminster, MD 21157
Rev. 10/2018

PACKAGE LABEL

Methylphenidate Hcl 10mg/5ml #500ml